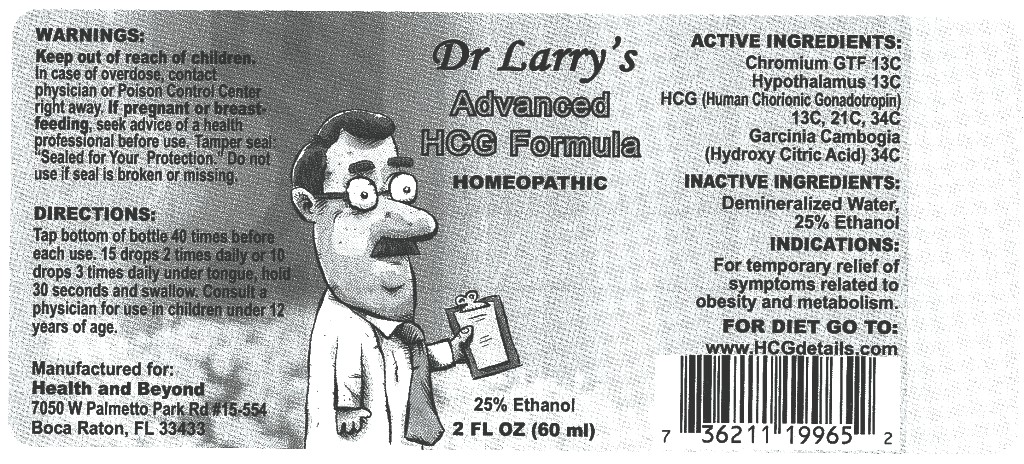 DRUG LABEL: Dr L Advanced HCG Formula
NDC: 57520-0576 | Form: LIQUID
Manufacturer: Apotheca Company
Category: homeopathic | Type: HUMAN OTC DRUG LABEL
Date: 20110215

ACTIVE INGREDIENTS: CHROMIUM PICOLINATE 13 [hp_C]/1 mL; SUS SCROFA HYPOTHALAMUS 13 [hp_C]/1 mL; HUMAN CHORIONIC GONADOTROPIN 34 [hp_C]/1 mL; GARCINIA CAMBOGIA FRUIT 34 [hp_C]/1 mL
INACTIVE INGREDIENTS: WATER; ALCOHOL

Dr L Advanced HCG Formula

ACTIVE INGREDIENT

ACTIVE INGREDIENTS: Chromium GTF 13C, Hypothalamus 13C, HCG (Human Chorionic Gonadotropin) 13C, 21C, 34C, Garcinia cambogia 34C.

PURPOSE

INDICATIONS: For temporary relief of symptoms related to obesity and metabolism.

WARNINGS

WARNINGS: Keep out of reach of children. In case of overdose, contact physician or Poison Control Center right away.

If pregnant or breast-feeding, seek advice of a health professional before use.

Tamper seal: "Sealed for Your Protection." Do not use if seal is broken or missing.

DOSAGE AND ADMINISTRATION

DIRECTIONS: Tap bottom of bottle 40 times before each use. 15 drops 2 times daily or 10 drops 3 times daily under tongue, hold 30 seconds and swallow. Consult a physician for use in children under 12 years of age.

INACTIVE INGREDIENTS: Demineralized water, 25% Ethanol.

KEEP OUT OF REACH OF CHILDREN. In case of overdose, contact physician or Poison Control Center right away.

INDICATIONS AND USAGE

INDICATIONS: For temporary relief of symptoms related to obesity and metabolism.

QUESTIONS

Manufactured for:

Health and Beyond

7050 W. Palmetto Park Rd #15-554

Boca Raton, FL 33433

FOR DIET GO TO:

www.HCGdetails.com

PACKAGE LABEL

Dr Larry's

ADVANCED HCG FORMULA

2 FL OZ (60 ml)